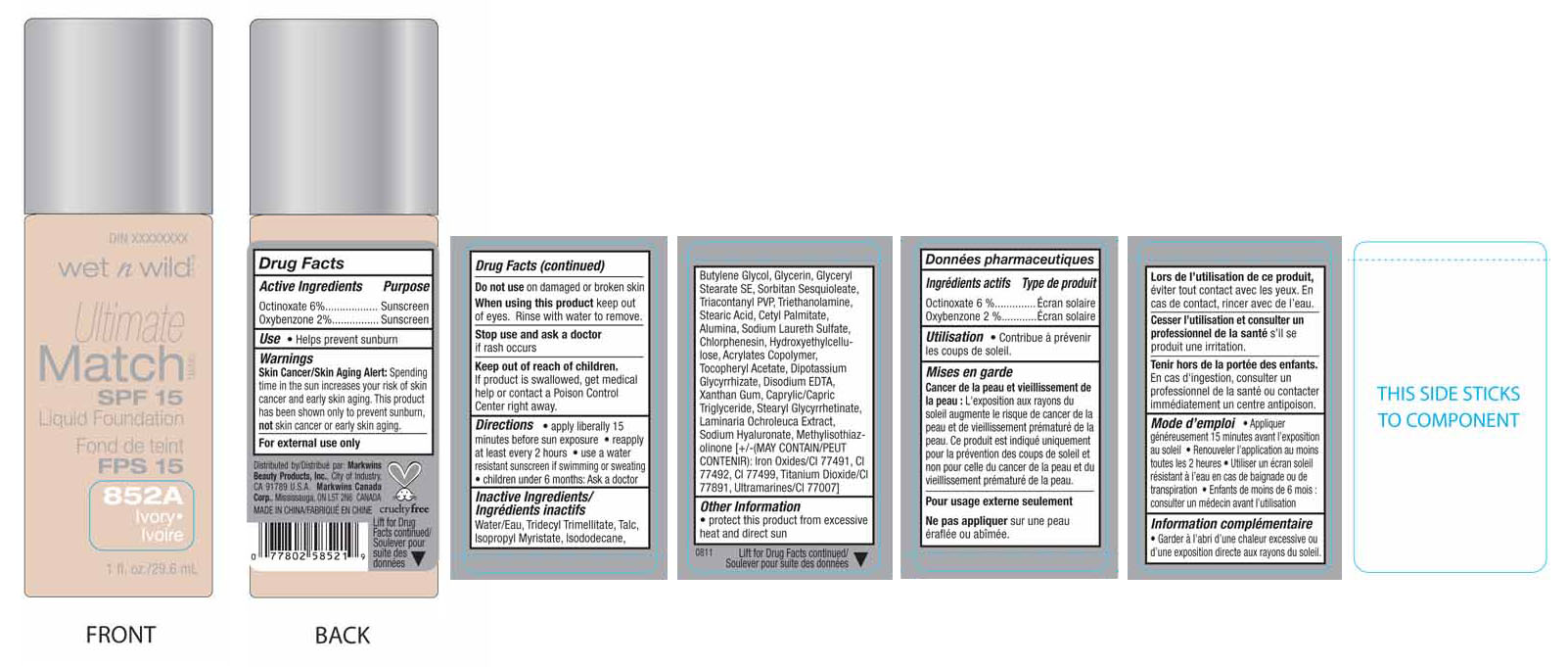 DRUG LABEL: wet n wild
NDC: 12027-102 | Form: LIQUID
Manufacturer: Markwins Beauty Products, Inc 
Category: otc | Type: HUMAN OTC DRUG LABEL
Date: 20111119

ACTIVE INGREDIENTS: OCTINOXATE 6 mL/100 mL; OXYBENZONE 2 mL/100 mL
INACTIVE INGREDIENTS: WATER; TRIDECYL TRIMELLITATE; TALC; ISOPROPYL MYRISTATE; ISODODECANE; BUTYLENE GLYCOL; GLYCERIN; GLYCERYL MONOSTEARATE; SORBITAN SESQUIOLEATE; TRIACONTANYL PVP (WP-660); TROLAMINE; STEARIC ACID; CETYL PALMITATE; ALUMINUM OXIDE; SODIUM LAURETH SULFATE; CHLORPHENESIN; DISODIUM GLYCYRRHIZATE; EDETATE DISODIUM; XANTHAN GUM; STEARYL GLYCYRRHETINATE; LAMINARIA OCHROLEUCA; HYALURONATE SODIUM; METHYLISOTHIAZOLINONE; FERRIC OXIDE RED; TITANIUM DIOXIDE

Active Ingredients
Octinoxate 6%
Oxybenzone 2%

INDICATIONS AND USAGE

Use• Helps prevent sunburn

Warnings
Skin Cancer/Skin Aging Alert: Spending time in the sun increases your risk of skin cancer and early skin aging. This product has been shown only to help prevent sunburn, not skin cancer or skin aging.
For external use only.
Do not use on damaged or broken skin
When using this product keep out of eyes. Rinse with water to remove.

Stop use and ask a doctor
if rash occurs

Keep out of reach of children.
If product is swallowed, get medical help or contact a Poison Control Center right away.

INDICATIONS AND USAGE

Directions • apply liberally 15 minutes before sun exposure • reapply at least every 2 hours
• use a water resistant sunscreen if swimming or sweating
• children under 6 months: Ask a doctor

INACTIVE INGREDIENT

Inactive Ingredients/Ingredients inactifs Water/Eau, Tridecyl Trimellitate, Talc, Isopropyl Myristate, Isododecane, Butylene Glycol, Glycerin, Glyceryl Stearate SE, Sorbitan Sesquioleate, Triacontanyl PVP, Triethanolamine, Stearic Acid, Cetyl Palmitate, Alumina, Sodium Laureth Sulfate, Chlorphenesin, Hydroxyethylcellulose, Acrylates Copolymer, Tocopheryl Acetate, Dipotassium Glycyrrhizate, Disodium EDTA, Xanthan Gum, Caprylic/Capric Triglyceride, Stearyl Glycyrrhetinate, Laminaria Ochroleuca Extract, Sodium Hyaluronate, Methylisothiazolinone
(MAY CONTAIN/PEUT CONTENIR): Iron Oxides/CI 77491, CI 77492, CI 77499, Titanium Dioxide/CI 77891, Ultramarines/CI 77007 77891, Yellow 6 Lake/CI 15985, Yellow 10 Lake/CI 47005, Zinc Oxide/CI 77947)

Package Label